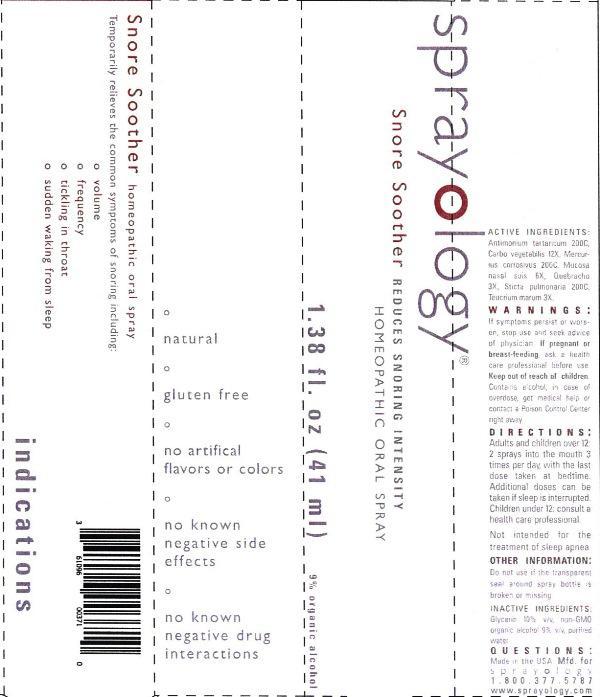 DRUG LABEL: Sprayology Snore Soother
NDC: 61096-0024 | Form: LIQUID
Manufacturer: Eight and Company
Category: homeopathic | Type: HUMAN OTC DRUG LABEL
Date: 20140318

ACTIVE INGREDIENTS: ANTIMONY POTASSIUM TARTRATE 200 [hp_C]/41 mL; ACTIVATED CHARCOAL 12 [hp_X]/41 mL; MERCURIC CHLORIDE 200 [hp_C]/41 mL; SUS SCROFA NASAL MUCOSA 6 [hp_X]/41 mL; ASPIDOSPERMA QUEBRACHO-BLANCO BARK 3 [hp_X]/41 mL; LOBARIA PULMONARIA 200 [hp_C]/41 mL; TEUCRIUM MARUM 3 [hp_X]/41 mL
INACTIVE INGREDIENTS: GLYCERIN; ALCOHOL; WATER

Sprayology Snore Soother

ACTIVE INGREDIENT

Active Ingredients: Antimonium tartaricum 200C, Carbo vegetabilis 12X, Mercurius corrosivus 200C, Mucosa nasalis suis 6X, Quebracho 3X, Sticta pulmonaria 200C, Teucrium marum 3X.

WARNINGS

Warnings: If symptoms persist or worsen, stop use and seek advice of physician. If pregnant or breast-feeding, ask a health care professional before use. Keep out of reach of children. Contains alcohol, in case of overdose, get medical help or contact a Poison Control Center right away.

Keep out of reach of children.

Directions:

- Adults and children over 12: 2 sprays into the mouth 3 times per day, with the last dose taken at bedtime. Additional doses can be taken if sleep is interrupted.
- Children under 12: consult a health care professional.
- Not intended for the treatment of sleep apnea.

PURPOSE

Temporarily relieves the common symptoms of snoring including:

- volume
- frequency
- tickling in throat
- sudden waking from sleep

Other Information: Do not use if the transparent seal around spray bottle is broken or missing.

INACTIVE INGREDIENT

Inactive Ingredients: Glycerin 10% v/v, non-GMO organic alcohol 9% v/v, purified water.

INDICATIONS AND USAGE

Temporarily relieves the common symptoms of snoring including:

° volume

° frequency

° tickling in throat

° sudden waking from sleep

° natural

° gluten free

° no artificial flavors or colors

° no known negative side effects

° no known negative drug interactions